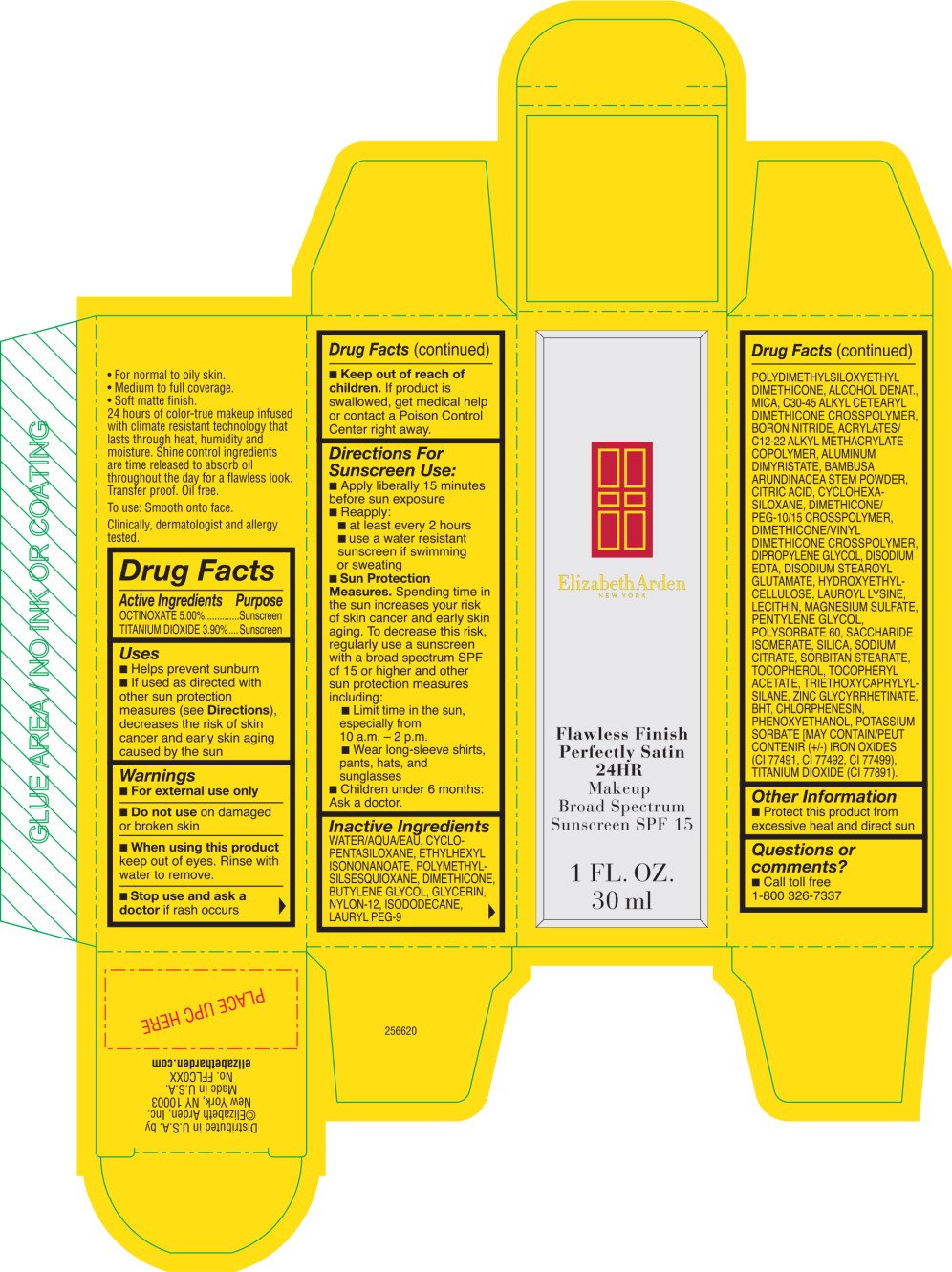 DRUG LABEL: FLAWLESS FINISH PERFECTLY SATINB 24HR MAKEUP SHADE 
NDC: 67938-2054 | Form: CREAM
Manufacturer: ELIZABETH ARDEN, INC
Category: otc | Type: HUMAN OTC DRUG LABEL
Date: 20150105

ACTIVE INGREDIENTS: OCTINOXATE 1.725 g/1 mL; TITANIUM DIOXIDE 1.346 g/1 mL
INACTIVE INGREDIENTS: WATER; CYCLOMETHICONE 5; ETHYLHEXYL ISONONANOATE; DIMETHICONE; BUTYLENE GLYCOL; MICA; GLYCERIN; ISODODECANE; NYLON-12; LAURYL PEG-9 POLYDIMETHYLSILOXYETHYL DIMETHICONE; ALCOHOL; BORON NITRIDE; PHENOXYETHANOL; MAGNESIUM SULFATE; SILICON DIOXIDE; LAUROYL LYSINE; EDETATE DISODIUM; CHLORPHENESIN; POLYSORBATE 60; SORBITAN MONOSTEARATE; ALUMINUM DIMYRISTATE; TRIETHOXYCAPRYLYLSILANE; DISODIUM STEAROYL GLUTAMATE; BAMBUSA BAMBOS STEM; CYCLOMETHICONE 6; PENTYLENE GLYCOL; DIPROPYLENE GLYCOL; CITRIC ACID MONOHYDRATE; SACCHARIDE ISOMERATE; .ALPHA.-TOCOPHEROL ACETATE; SODIUM CITRATE; POTASSIUM SORBATE; BUTYLATED HYDROXYTOLUENE; TOCOPHEROL; FERRIC OXIDE YELLOW; FERRIC OXIDE RED; FERROSOFERRIC OXIDE

Drug Facts

Active Ingredients

OCTINOXATE 5.00%

TITANIUM DIOXIDE 3.90%

Purpose

Sunscreen

Sunscreen

Uses

- Helps prevent sunburn
- If used as directed with other sun protection measures (see Directions), decreases the risk of skin cancer and early skin aging caused by the sun

Warnings

- For external use only

- Do not use on damaged or broken skin

- When using this product keep out of eyes. Rinse with water to remove.

- Stop use and ask a doctor if rash occurs

- Keep out of reach of children. If product is swallowed, get medical help or contact a Poison Control Center right away.

Directions For Sunscreen Use:

- Apply liberally 15 minutes before sun exposure
- Reapply:
  - at least every 2 hours
  - use a water resistant sunscreen if swimming or sweating
- Sun Protection Measures. Spending time in the sun increases your risk of skin cancer and early skin aging. To decrease this risk, regularly use a sunscreen with a broad spectrum SPF of 15 or higher and other sun protection measures including:
  - Limit time in the sun, especially from 10 a.m. -2 p.m.
  - Wear long-sleeve shirts, pants, hats, and sunglasses
- Children under 6 months: Ask a doctor.

Inactive Ingredients

WATER/AQUA/EAU, CYCLO- PENTASILOXANE, ETHYLHEXYL ISONONANOATE, POLYMETHYL- SILSESQUIOXANE, DIMETHICONE, BUTYLENE GLYCOL, GLYCERIN, NYLON-12, ISODODECANE, LAURYL PEG-9 POLYDIMETHYLSILOXYETHYL DIMETHICONE, ALCOHOL DENAT., MICA, C30-45 ALKYL CETEARYL DIMETHICONE CROSSPOLYMER, BORON NITRIDE, ACRYLATES/C12-22 ALKYL METHACRYLATE COPOLYMER, ALUMINUM DIMYRISTATE, BAMBUSA ARUNDINACEA STEM POWDER, CITRIC ACID, CYCLOHEXA- SILOXANE, DIMETHICONE/ PEG-10/15 CROSSPOLYMER, DIMETHICONE/VINYL DIMETHICONE CROSSPOLYMER, DIPROPYLENE GLYCOL DISODIUM EDTA, DISODIUM STEAROYL GLUTAMATE, HYDROXYETHYL- CELLULOSE, LAUROYL LYSINE, LECITHIN, MAGNESIUM SULFATE, PENTYLENE GLYCOL, POLYSORBATE 60, SACCHARIDE ISOMERATE, SILICA, SODIUM CITRATE, SORBITAN STEARATE, TOCOPHEROL, TOCOPHERYL ACETATE, TRIETHOXYCAPRYLYL- SILANE, ZINC GLYCYRRHETINATE, BHT, CHLORPHENESIN, PHENOXYETHANOL, POTASSIUM SORBATE [MAY CONTAIN/PEUT CONTENIR (+/-) IRON OXIDES (Cl 77491, Cl 77492, Cl 77499), TITANIUM DIOXIDE (Cl 77891).

Other Information

- Protect this product from excessive heat and direct sun

Questions or comments?

- Call toll free 1-800 326-7337

Principal Display Panel - Box Label

Elizabeth Arden
NEW YORK

Flawless Finish
Perfectly Satin
24HR

Makeup

Broad Spectrum

Sunscreen SPF 15

1 FL. OZ.

30 ml